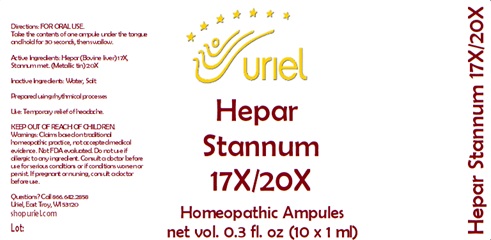 DRUG LABEL: Hepar Stannum 17/20
NDC: 48951-5045 | Form: LIQUID
Manufacturer: Uriel Pharmacy Inc.
Category: homeopathic | Type: HUMAN OTC DRUG LABEL
Date: 20241213

ACTIVE INGREDIENTS: MAMMAL LIVER 17 [hp_X]/1 mL; TIN 20 [hp_X]/1 mL
INACTIVE INGREDIENTS: WATER; SODIUM CHLORIDE

Hepar Stannum 17/20

INDICATIONS AND USAGE

Directions: FOR ORAL USE ONLY.

DOSAGE AND ADMINISTRATION

Take the contents of one ampule
under the tongue and hold for
30 seconds, then swallow.

ACTIVE INGREDIENT

Active Ingredients: Hepar (Bovine liver) 17X, Stannum met. (Metallic tin) 20X

Inactive Ingredients: Water, Salt

Prepared using rhythmical processes.

PURPOSE

Use: Temporary relief of headache.

KEEP OUT OF REACH OF CHILDREN.

WARNINGS

Warnings: Claims based on traditional homeopathic practice, not accepted medical evidence. Not FDA evaluated. Do not use if allergic to any ingredient. Consult a doctor before use for serious conditions or if conditions worsen or persist. If pregnant or nursing, consult a doctor before use.

Questions? Call 866.642.2858
Uriel, East Troy, WI 53120
shopuriel.com Lot: